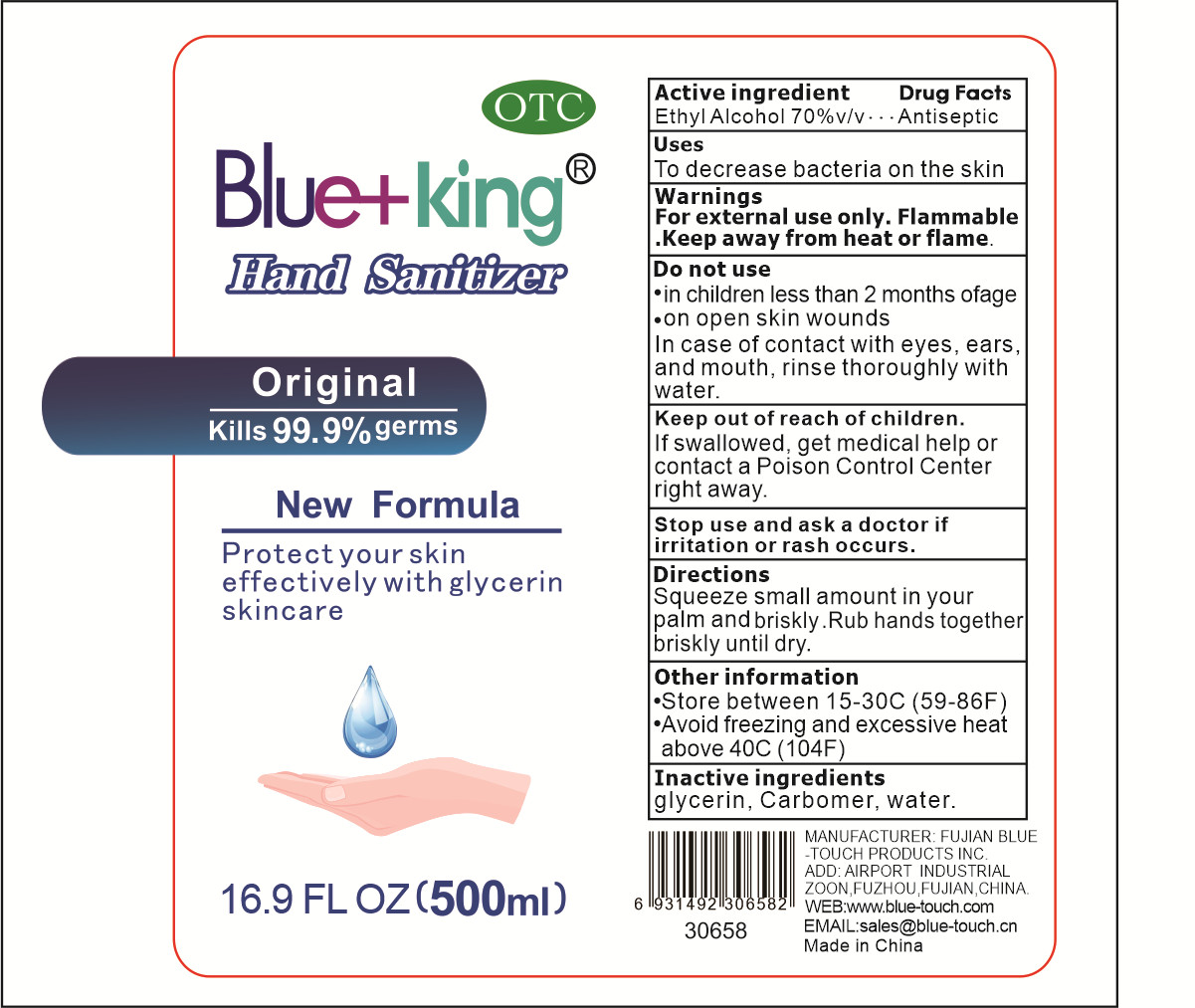 DRUG LABEL: Hand Sanitizer
NDC: 52578-004 | Form: LIQUID
Manufacturer: FUJIAN BLUE-TOUCH PRODUCTS INC.
Category: otc | Type: HUMAN OTC DRUG LABEL
Date: 20200525

ACTIVE INGREDIENTS: ALCOHOL 350 mL/500 mL
INACTIVE INGREDIENTS: GLYCERIN; WATER; CARBOMER HOMOPOLYMER, UNSPECIFIED TYPE

DOSAGE AND ADMINISTRATION

1.Store between 15-30°C (59-86F)
2.Avoid freezing and excessive heat above 40°C (104F)

INACTIVE INGREDIENT

WATER

CARBOMER

GLYCERIN

INDICATIONS AND USAGE

Squeeze small amount in your palm and briskly .Rub hands together briskly until dry.

ACTIVE INGREDIENT

ETHYL ALCOHOL

keep out of reach of children

PURPOSE

Disinfection
Sterilization
No Rinseing

WARNINGS

For external use only. Flammable.Keep away from heat or flame.